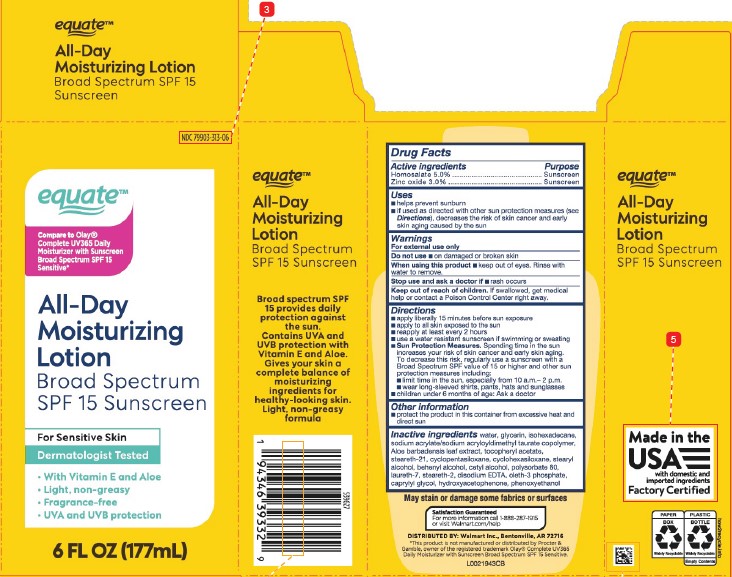 DRUG LABEL: All Day Moisture
NDC: 79903-313 | Form: LOTION
Manufacturer: Walmart Inc.
Category: otc | Type: HUMAN OTC DRUG LABEL
Date: 20260211

ACTIVE INGREDIENTS: HOMOSALATE 50 mg/1 mL; ZINC OXIDE 30 mg/1 mL
INACTIVE INGREDIENTS: WATER; GLYCERIN; ISOHEXADECANE; SODIUM ACRYLATE/SODIUM ACRYLOYLDIMETHYLTAURATE COPOLYMER (4000000 MW); ALOE VERA LEAF; .ALPHA.-TOCOPHEROL ACETATE; STEARETH-21; CYCLOMETHICONE 5; CYCLOMETHICONE 6; STEARYL ALCOHOL; DOCOSANOL; CETYL ALCOHOL; POLYSORBATE 80; LAURETH-7; STEARETH-2; EDETATE DISODIUM ANHYDROUS; OLETH-3 PHOSPHATE; CAPRYLYL GLYCOL; HYDROXYACETOPHENONE; PHENOXYETHANOL

Equate 227.000/227AA
Complete Beauty Lotion SPF 15

Active ingredients

Homosalate 5.0%

Zinc oxide 3.0%

Purpose

Sunscreen

Uses

- helps prevent sunburn
- if used as directed with other sun protection measures (see Directions), decreases the risk of skin cancer and early skin aging caused by the sun

Warnings

For external use only

Do not use

- on damaged or broken skin

When using this product

- keep out of eyes. Rinse with water to remove.

Stop use and ask a doctor if

- rash occurs

Keep out of reach of children.

If swallowed, get medical help or contact a Poison Control Center right away.

Directions

- apply liberally 15 minutes before sun exposure
- apply to all skin exposed to the sun
- reapply at least every 2 hours
- use a water resistant sunscreen if swimming or sweating
- Sun Protection Measures. Spending time in the sun increases your risk of skin cancer and early skin aging. To decrease this risk, regularly use a sunscreen with a Broad Spectrum SPF value of 15 or higher and other sun protection measures including:
- limit time in the sun, especially from 10 a.m.–2 p.m.
- wear long-sleeved shirts, pants, hats and sunglasses
- children under 6 months of age: Ask a doctor

Other information

- protect the product in this container from excessive heat and direct sun

Inactive ingredients

water, glycerin, isohexadecane, sodium acrylate/sodium acryloyldimethyl taurate copolymer, Aloe barbadensis leaf extract, tocopheryl acetate, steareth-21, cyclopentasiloxane, cyclohexasiloxane, stearyl alcohol, behenyl alcohol, cetyl alcohol, polysorbate 80, laureth-7, steareth-2, disodium EDTA, oleth-3 phosphate, caprylyl glycol, hydroxyacetophenone, phenoxyethanol

Disclaimer

May stain or damage some fabrics or surfaces

Side panel claims

equate ™

ALL-DAY

MOISTURIZING LOTION

Broad Spectrum SPF 15 Sunscreen

Broad spectrum SPF 15 provides daily protection against the sun. Contains UVA and UVB protection with Vitamin E and Aloe. Gives your skin a complete balance of moisturizing ingredients for healthy-looking skin. Light, non-greasy formula.

Made in the USA with domestic and imported ingredients

Factory Certified

PAPER BOX

Widely Recyclable

PLASTIC BOTTLE

Widely Recyclable

Empty Contents

how2recycle.info

Adverse Reaction

Satisfaction Guaranteed

For more information call 1-888-287-1915 or visit Walmart.com/help

DISTRIBUTED BY: Walmart Inc., Bentonville, AR 72716

Disclaimer

*This product is not manufactured or distributed by Procter & Gamble, owner of the registered trademark OlayComplete UV365 Daily Moisturizer with Sunscreen Broad Spectrum SPF 15 Sensitive.

Principal Display Panel

NDC 79903-313-06

equate™

Compare to Olay® Complete UV365 Daily Moisturizer with Sunscreen Broad Spectrum SPF 15 Sensitive*

ALL-DAY MOISTURIZING LOTION

Broad Spectrum SPF 15 Sunscreen

For Sensitive Skin

Dermatologist Tested

- With Vitamin E and Aloe
- Light, Non-Greasy
- Fragrance-Free
- UVA and UVB protection

6 FL OZ (177 mL)